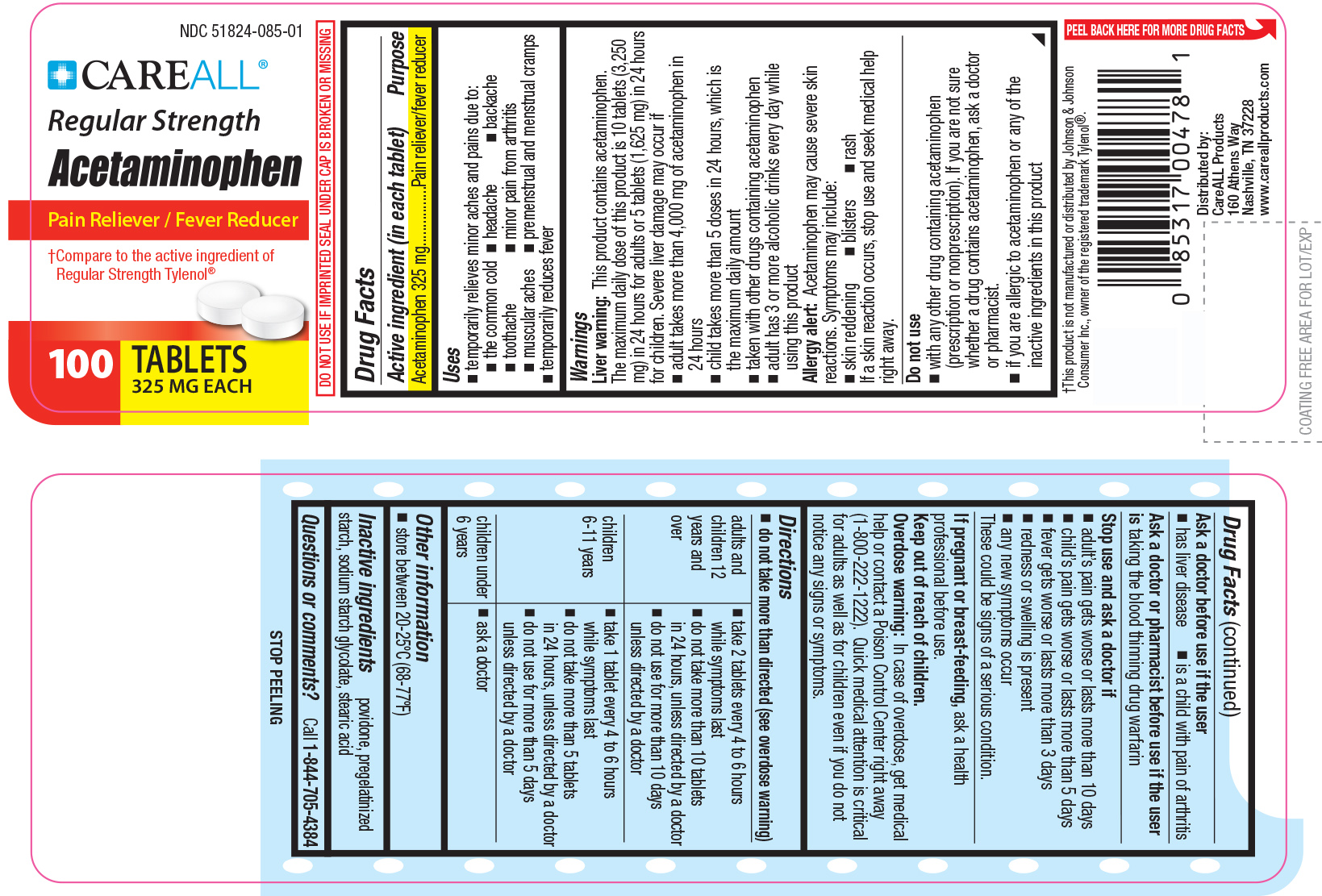 DRUG LABEL: CareALL Acetaminophen
NDC: 51824-085 | Form: TABLET
Manufacturer: New World Imports, Inc
Category: otc | Type: HUMAN OTC DRUG LABEL
Date: 20251222

ACTIVE INGREDIENTS: ACETAMINOPHEN 325 mg/1 1
INACTIVE INGREDIENTS: STARCH, CORN; STEARIC  ACID; POVIDONE; SODIUM STARCH GLYCOLATE TYPE A CORN

Drug Facts

Active Ingredient

Acetaminophen 325mg

Purpose

Pain reliever / Fever reducer

Keep out of Reach of Children

Overdose warning:In case of overdose, get medical help or contact a Poison Control Center immediately (1-800-222-1222). Quick medical attention is critical for adults as well as for chidren even if you do not notice any signs or symptoms.

Uses

Temporary relieves minor aches and pains due to: the common cold, headache, toothache, muscular aches, backache, minor pain of arthritis, premenstrual and menstrual cramps.

Temporarily reduces fever

WARNINGS

Liver warning:This product contains acetaminophen. The maximum daily dose of this product is 10 tablets (3,250mg) in 24 hours for adults or 5 tablets (1,625mg) in 24 hours for children. Severe liver damage may occur if:

Adult takes more than 4,000mg of acetaminphen in 24 hours

Child takes more than 5 doses in 24 hours, which is the maximum daily amount

Taken with other drugs containing acetaminophen

Adult has 3 or more alcoholic drinks every day while using this product

Allergy Alert:Acetaminophen may cause severe skin reactions. Symptoms may include: skin reddening, blisters or rash. If a skin reaction occurs, stop use and seek medical help right away.

Do not use:

With any other drug containing acetaminophen (prescription or nonprescription) If you are not sure whether a drug contains acetaminophen, ask a doctor or pharmacist.

If you are allergic to acetaminophen or any of the inactive ingredients in this product.

Ask a doctor before use if user has:

liver disease

is a child with pain of arthritis

Ask a doctor or pharmacist before use if:the user is taking the blood thinnig drug warfarin.

Stop use and ask a doctor if:

Adult's pain gets worse or lasts for more than 10 days.

Child's pain gets worse or lasts more than 5 days.

Fever gets worse or lasts for more than 3 days.

Redness or swelling is present.

New symptoms occur.

These could be signs of a serious condition.

If pregnant or breast-feeding,ask a health professional before use.

DOSAGE AND ADMINISTRATION

Adults and children 12 years and over:

Take 2 tablets every 4 to 6 hours while symptoms last

Do not take more than 10 tablets in 24 hours, unless directed by a doctor.

Do not use for more than 10 days unless directed by a doctor

Children 6-11 years:

Take 1 tablet every 4 to 6 hours while symptoms last.

Do not take more than 5 tablets in 24 hours, unless directed by a doctor.

Do not use for more than 5 days unless directed by a doctor

Children under 6 years of age:Ask a doctor

INACTIVE INGREDIENT

povidone, pregelatinized starch, sodium starch glycolate, stearic acid